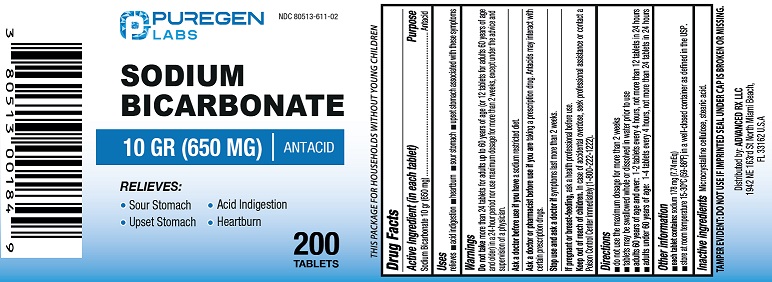 DRUG LABEL: Sodium Bicarbonate


NDC: 80513-611 | Form: TABLET
Manufacturer: Advanced Rx LLC
Category: otc | Type: HUMAN OTC DRUG LABEL
Date: 20250901

ACTIVE INGREDIENTS: SODIUM BICARBONATE 650 mg/1 1
INACTIVE INGREDIENTS: MICROCRYSTALLINE CELLULOSE; STEARIC ACID

Active ingredient (in each tablet)

Sodium bicarbonate 10 gr (650 mg)

Purpose

Antacid

Uses

Relieves

- acid indigestion
- heartburn
- sour stomach
- upset stomach associated with these symptoms

WARNINGS

- Do not takemore than 24 tablets for adults up to 60 years of age (or 12 tablets for adults 60 years of age and older) in a 24 hour period nor use maximum dosage for more than 2 weeks, except under the advice and supervision of a physician.

Ask a doctor before use if you have

a sodium restricted diet.

Ask a doctor or pharmacist before use if you are

taking a presciption drug. Antacids may intract with certain prescription drugs.

Stop use and ask a doctor if

symptoms last more than 2 weeks.

If pregnant or breast-feeding,

ask a health professional before use.

Keep out of reach of children.

In case of accidental overdose, seek professional assistance or contact a Poison Control Center immediately (1-800-222-1222).

Directions

- Do not use the maximum dosage for more than 2 weeks
- tablets may be swallowed whole or dissolved in water prior to use
- adults 60 years of age and over: 1-2 tablets every 4 hours, not more than 12 tablets in 24 hours
- adults under 60 years of age: 1-4 tablets every 4 hours, not more than 24 tablets in 24 hours

Other information

- each tablet contains: sodium 178 mg (7.74 mEq)
- store at room temperature 15-30°C (59-86°F) in well-closed container as defined in the USP.

Inactive ingredients

Microcrystalline cellulose, stearic acid.

TEMPER EVIDENT: DO NOT USE IF IMPRINTED SEAL UNDER CAP IS BROKEN OR MISSING.

Distributed by:

ADVANCED RX LLC

1942 NE 163rd St North Miami Beach,

FL33162 U.S.A